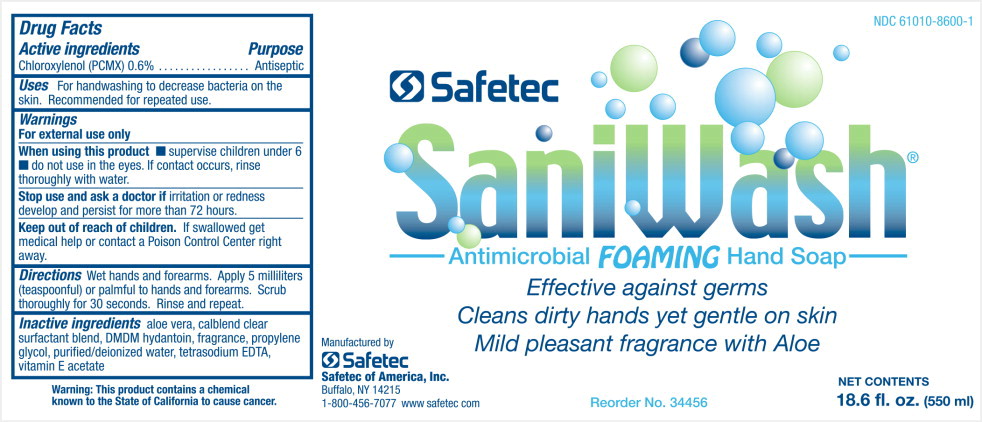 DRUG LABEL: Saniwash Antimicrobial Foaming Hand
NDC: 61010-8600 | Form: LIQUID
Manufacturer: Safetec of America, Inc.
Category: otc | Type: HUMAN OTC DRUG LABEL
Date: 20240204

ACTIVE INGREDIENTS: CHLOROXYLENOL 0.006 g/1 mL
INACTIVE INGREDIENTS: ALOE VERA LEAF; SODIUM LAURETH-3 SULFATE; COCO DIETHANOLAMIDE; COCAMIDOPROPYL BETAINE; DMDM HYDANTOIN; PROPYLENE GLYCOL; WATER; EDETATE SODIUM; .ALPHA.-TOCOPHEROL ACETATE

61010-8600-1, SaniwashAntimicrobial Foming Hand

Active Ingredient

Chloroxylenol (PCMX)

Purpose

Antiseptic

Uses

- For hand washing to decrease bacteria on the skin.
- Recommended for repeated use

Warnings

For external use only.

When using this product

- supervise children under 6
- do not use in eyes. If contact occurs, rinse thoroughly with water.

Stop use and ask doctor ifirritation or redness develop and persists for more than 72 hours.

Keep out of reach of children.If swallowed get medical help or contact a Poison Control Center right away

Directions

Wet hands and forearms. Apply 5 millimeters (teaspoonful) or palmful to hand and forearm. Scrub thoroughly for 30 seconds. Rince and repeat.

Inactive ingredients

aloe vera, calblend clear surfactant blend, DMDM hydantoin, fragrance, propylene glycol, purified/deionized water, tetrasodium EDTA, vitamin E acetate

PRINCIPAL DISPLAY PANEL -18.6 fl. oz

NDC 61010-8600-1

Safetec

Saniwash

Antimicrobial Foaming Hand Soap

Effective against germs

Cleans dirty hands yet gentle on skin

Mild pleasant fragrance with Aloe

Manufactured by

Safetec

Safetec of America, Inc

Buffalo, NY 14215

1-800-456-7077 www.safetec.com Reorder No. 34456 Net Contents

18.6 fl. Oz (550 ml)